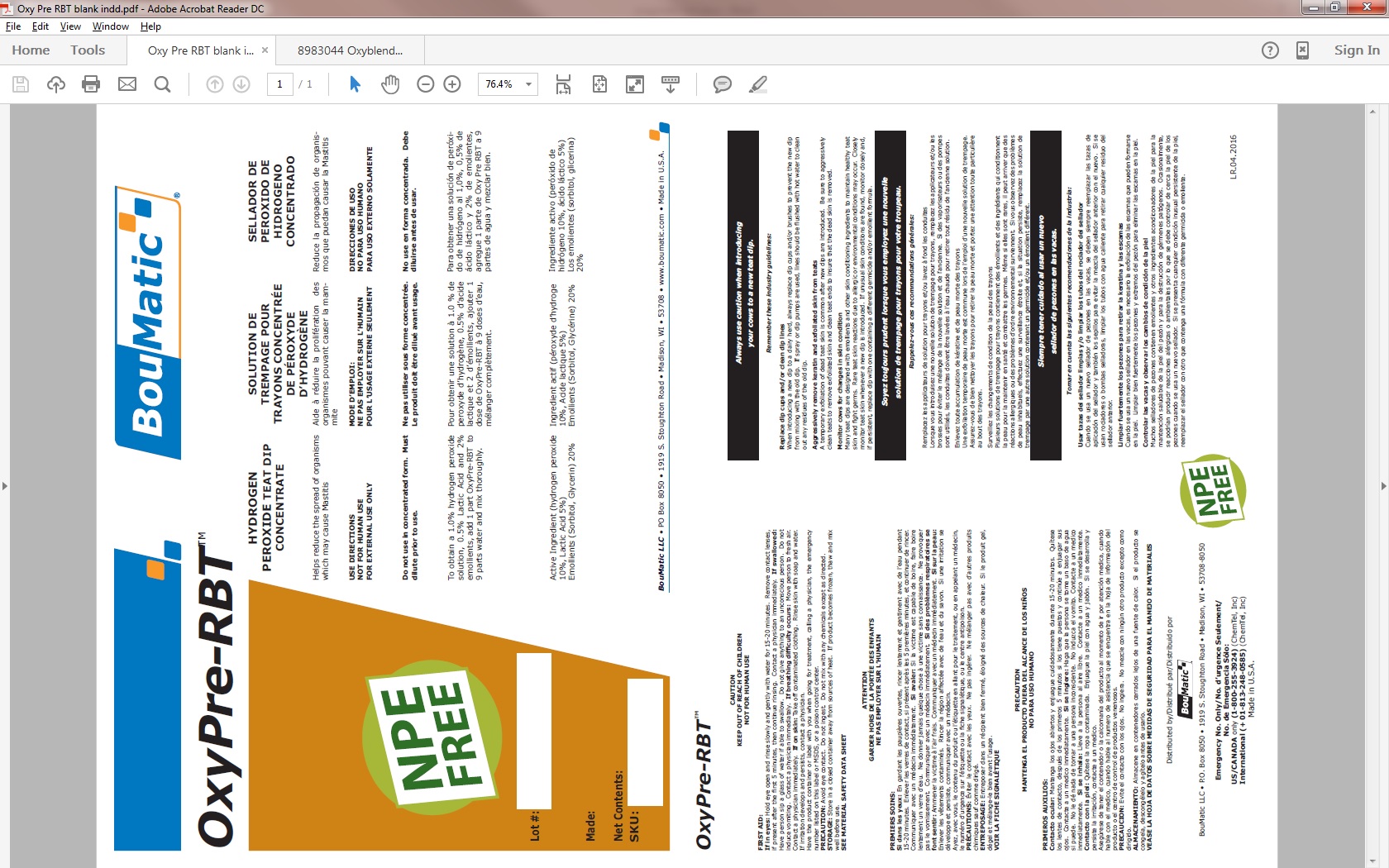 DRUG LABEL: OxyPre-RBT
NDC: 48106-2020 | Form: LIQUID
Manufacturer: BouMatic, LLC
Category: animal | Type: OTC ANIMAL DRUG LABEL
Date: 20240614

ACTIVE INGREDIENTS: HYDROGEN PEROXIDE 100 g/1 L; LACTIC ACID 50 g/1 L

OxyPre-RBT

WARNINGS AND PRECAUTIONS

CAUTION

KEEP OUT OF REACH OF CHILDREN

NOT FOR HUMAN USE

FIRST AID:

If in eyes: Hold eye open and rinse slowly and gently with water for 15-20 minutes. Remove contact lenses, if present after the first 5 minutes, then continue rinsing. Contact a physician immediately. If swallowed: Have person sip a glass of water if able to swallow. Do not give anything to an unconscious person. Do not induce vomiting. Contact a physician immediately. If breathing difficulty occurs: Move person to fresh air. Contact a physician immediately. If on skin: Take off contaminated clothing. Rinse skin with soap and water. If irritation develops and persists, contact a physician.

Have the product container or label with you when going for treatment, calling a physician, the emergency number listed on this label or MSDS, or a poison control center.

PRECAUTION: Avoid eye contact. Do not ingest. Do not mix with any chemicals except as directed.

STORAGE: Store in a closed container away from sources of heat. If product becomes frozen, thaw and mix well before use.

SEE MATERIAL SAFETY DATA SHEET

INDICATIONS AND USAGE

OxyPre-RBT

HYDROGEN PEROXIDE TEAT DIP CONCENTRATE

Helps reduce the spread of organisms which may cause Mastitis

USE DIRECTIONS

NOT FOR HUMAN USE

FOR EXTERNAL USE ONLY

Do not use in concentrated form.

Must dilute prior to use.

To obtain a 1.0% hydrogen peroxide solution, 0.5% Lactic Acid and 2% emollients, add 1 part OxyPre-RBT to 9 parts water and mix thoroughly.

Active Ingredient (hydrogen peroxide 10%, Lactic Acid 5%)

Emollients (Sorbitol, Glycerin) 20%